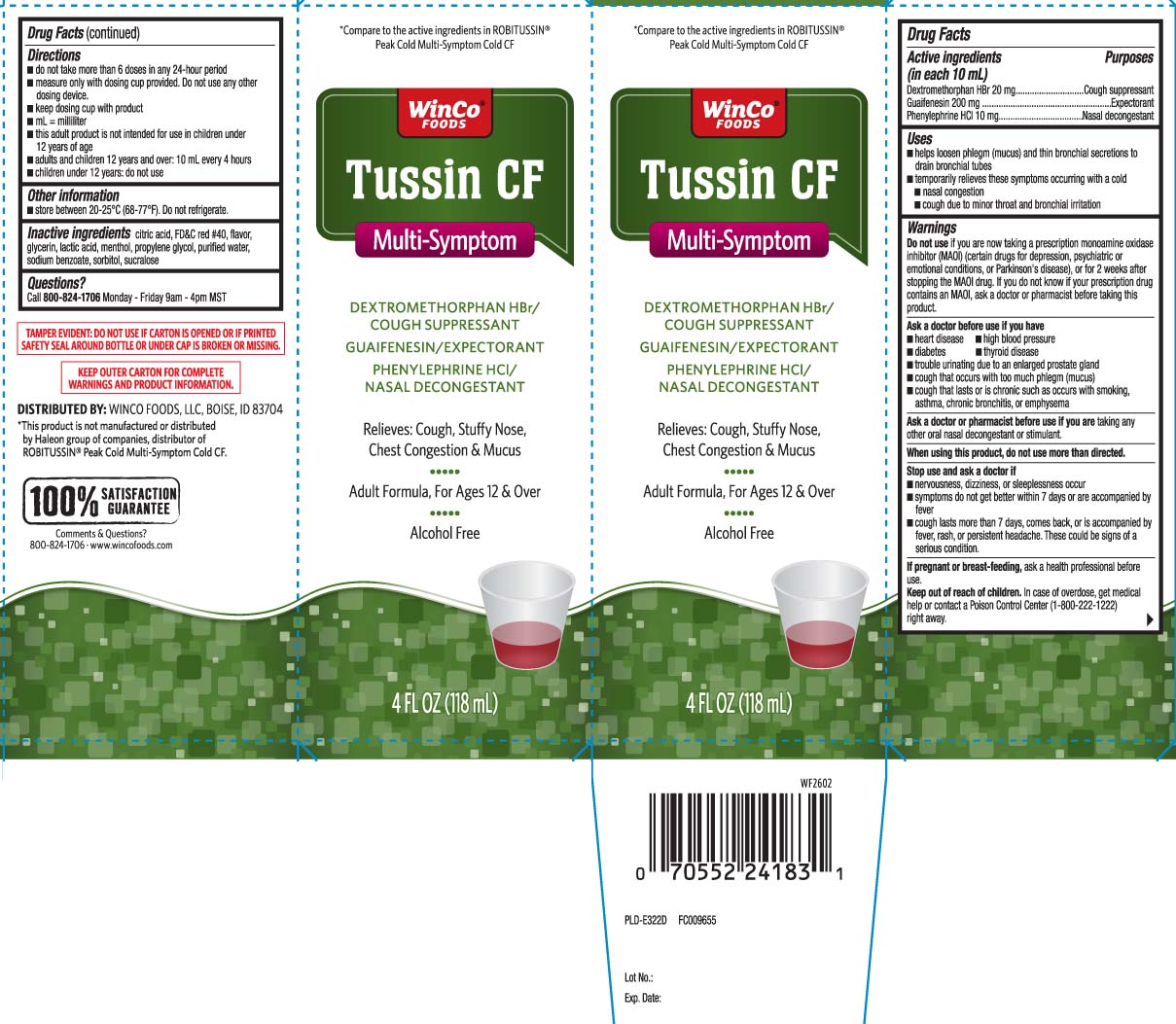 DRUG LABEL: Tussin CF
NDC: 67091-470 | Form: LIQUID
Manufacturer: WinCo Foods, LLC
Category: otc | Type: HUMAN OTC DRUG LABEL
Date: 20260225

ACTIVE INGREDIENTS: DEXTROMETHORPHAN HYDROBROMIDE 20 mg/10 mL; GUAIFENESIN 200 mg/10 mL; PHENYLEPHRINE HYDROCHLORIDE 10 mg/10 mL
INACTIVE INGREDIENTS: ANHYDROUS CITRIC ACID; GLYCERIN; PROPYLENE GLYCOL; WATER; SODIUM BENZOATE; FD&C RED NO. 40; LACTIC ACID; MENTHOL; SORBITOL; SUCRALOSE

Drug Facts

Active ingredients (in each 10 mL)

Dextromethorphan HBr 20 mg

Guaifenesin 200 mg

Phenylephrine HCl 10 mg

Purposes

Cough suppressant

Expectorant

Nasal decongestant

Uses

- helps loosen phlegm (mucus) and thin bronchial secretions to drain bronchial tubes
- temporarily relieves these symptoms occurring with a cold:
  - nasal congestion
  - cough due to minor throat and bronchial irritation

Warnings

Do not use

- if you are now taking a prescription monoamine oxidase inhibitor (MAOI) (certain drugs for depression, psychiatric or emotional conditions, or Parkinson’s disease), or for 2 weeks after stopping the MAOI drug. If you do not know if your prescription drug contains an MAOI, ask a doctor or pharmacist before taking this product.

Ask a doctor before use if you have

- heart disease
- diabetes
- high blood pressure
- thyroid disease
- cough that lasts or is chronic such as occurs with smoking, asthma, chronic bronchitis or emphysema
- cough that occurs with too much phlegm (mucus)
- trouble urinating due to enlarged prostate gland

Ask a doctor or pharmacist before use if you are

taking any other oral nasal decongestant or stimulant.

When using this product,

do not use more than directed.

Stop use and ask a doctor if

- nervousness, dizziness, or sleeplessness occur
- symptoms do not get better within 7 days or are accompanied by fever
- cough lasts more than 7 days, comes back, or is accompanied by fever, rash, or persistent headache.These could be signs of a serious condition.

If pregnant or breast-feeding,

ask a health professional before use.

Keep out of reach of children.

In case of overdose, get medical help or contact a Poison Control Center (1800-222-122) right away.

Directions

- do not take more than 6 doses in any 24-hour period
- measure only with dosing cup provided. Do not use any other dosing device.
- keep dosing cup with product
- mL = milliliter
- this adults product is not intended for use in children under 12 years of age
- adult and children 12 years and over: 10 mL every 4 hours
- children under 12 years: do not use

Other information

- store between 20-25°C (68-77°F). Do not refrigerate.

Inactive ingredients

anhydrous citric acid, FD&C red #40, flavor, glycerin, lactic acid, menthol, propylene glycol, purified water, sodium benzoate, sorbitol, sucralose

Questions?

Call 800-824-1706 Monday-Friday 9am-4pm MST

Principal Display Panel

*Compare to the active ingredients in ROBITUSSIN® Peak Cold Multi-Symptom Cold CF

Tussin CF

Multi-Symptom

DEXTROMETHORPHAN HBr / COUGH SUPPRESSANT

GUAIFENESIN / EXPECTORANT

PHENYLEPHRINE HCI / NASAL DECONGESTANT

Relieves: Cough, Stuffy Nose, Chest Congestion & Mucus

Adult Formula, For Ages 12 & Over

Alcohol Free

FL OZ (mL)

*This product is not manufactured or distributed by Haleon group of companies, distributors of ROBITUSSIN® Peak Cold Multi-Symptom Cold CF.

TAMPER EVIDENT: DO NOT USE IF CARTON IS OPENED OR IF PRINTED SAFETY SEAL AROUND BOTTLE OR UNDER CAP IS BROKEN OR MISSING.

KEEP OUTER CARTON FOR COMPLETE WARNINGS AND PRODUCT INFORMATION.

DISTRIBUTED BY: WINCO FOODS, LLC, BOISE, ID 83704

www.wincofoods.com

Package Label

WINCO Tussin CF Multi-Symptom